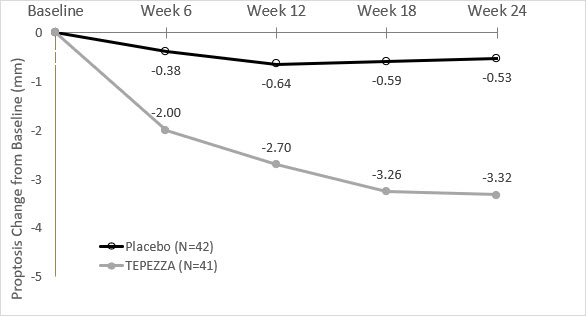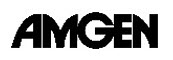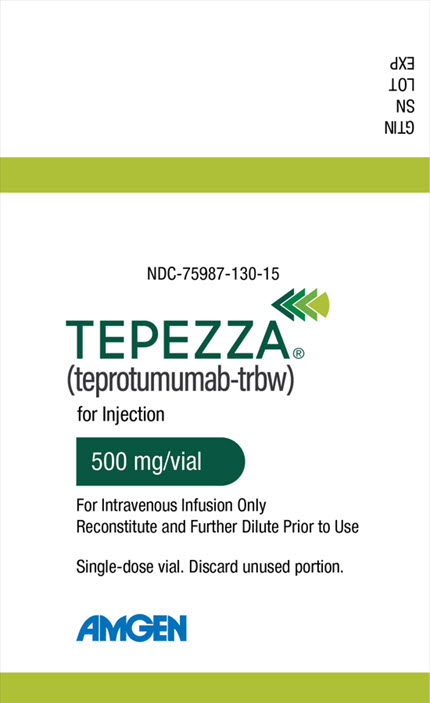 DRUG LABEL: TEPEZZA
NDC: 75987-130 | Form: INJECTION, POWDER, LYOPHILIZED, FOR SOLUTION
Manufacturer: Horizon Therapeutics USA, Inc.
Category: prescription | Type: HUMAN PRESCRIPTION DRUG LABEL
Date: 20251110

ACTIVE INGREDIENTS: TEPROTUMUMAB 500 mg/1 1
INACTIVE INGREDIENTS: HISTIDINE 7.45 mg/1 1; HISTIDINE MONOHYDROCHLORIDE MONOHYDRATE; POLYSORBATE 20; TREHALOSE DIHYDRATE

HIGHLIGHTS OF PRESCRIBING INFORMATION

These highlights do not include all the information needed to use TEPEZZA® safely and effectively. See full prescribing information for TEPEZZA.
TEPEZZA (teprotumumab-trbw) for injection, for intravenous use
Initial U.S. Approval: 2020

RECENT MAJOR CHANGES

Dosage and Administration, Administration (2.3) | 9/2025
Warnings, and Precautions, Inflammatory Bowel Disease (5.2) | 8/2025

1 INDICATIONS AND USAGE

TEPEZZA is an insulin-like growth factor-1 receptor inhibitor indicated for the treatment of Thyroid Eye Disease (1)

2 DOSAGE AND ADMINISTRATION

- Initiate dosing with 10 mg/kg for first infusion, followed by 20 mg/kg every 3 weeks for 7 additional infusions (2.1)
- Administer TEPEZZA by intravenous infusion over 60 to 90 minutes (2.3)

3 DOSAGE FORMS AND STRENGTHS

For Injection: 500 mg lyophilized powder in a single-dose vial for reconstitution (3)

4 CONTRAINDICATIONS

None (4)

5 WARNINGS AND PRECAUTIONS

- Infusion Reactions: If an infusion reaction occurs, interrupt or slow the rate of infusion and use appropriate medical management (5.1)
- Inflammatory Bowel Disease (IBD): Monitor patients; for signs and symptoms of disease, including patients without a history of IBD; discontinue TEPEZZA if IBD exacerbation is suspected (5.2)
- Hyperglycemia: Assess patients for elevated blood glucose and symptoms of hyperglycemia prior to infusion and continue to monitor while on treatment with TEPEZZA. Ensure patients with hyperglycemia or preexisting diabetes are under appropriate glycemic control before and while receiving TEPEZZA (5.3)
- Hearing Impairment Including Hearing Loss: TEPEZZA may cause severe hearing impairment including hearing loss, which in some cases may be permanent. Assess patients' hearing before, during, and after treatment with TEPEZZA and consider the benefit-risk of treatment with patients (5.4)

6 ADVERSE REACTIONS

Most common adverse reactions (incidence greater than 5%) are muscle spasm, nausea, alopecia, diarrhea, fatigue, hyperglycemia, hearing impairment, dry skin, dysgeusia, headache, weight decreased, and nail disorder (6.1)

To report SUSPECTED ADVERSE REACTIONS, contact Amgen Inc. at 1-800-77-AMGEN (1-800-772-6436) or FDA at 1-800-FDA-1088 or www.fda.gov/medwatch.

8 USE IN SPECIFIC POPULATIONS

Females of Reproductive Potential: Appropriate forms of contraception should be implemented prior to initiation, during treatment and for 6 months following the last dose of TEPEZZA (8.3)

FULL PRESCRIBING INFORMATION

1 INDICATIONS AND USAGE

TEPEZZA is indicated for the treatment of Thyroid Eye Disease regardless of Thyroid Eye Disease activity or duration.

2 DOSAGE AND ADMINISTRATION

2.1 Recommended Dosing

The recommended dose of TEPEZZA is an intravenous infusion of 10 mg/kg for the initial dose followed by an intravenous infusion of 20 mg/kg every three weeks for 7 additional infusions.

2.2 Reconstitution and Preparation

Step 1: Calculate the dose (mg) and determine the number of vials needed for the 10 or 20 mg/kg dosage based on patient weight. Each TEPEZZA vial contains 500 mg of the teprotumumab antibody.

Step 2: Using appropriate aseptic technique, reconstitute each TEPEZZA vial with 10 mL of Sterile Water for Injection, USP. Ensure that the stream of diluent is not directed onto the lyophilized powder, which has a cake-like appearance. Do not shake, but gently swirl the solution by rotating the vial until the lyophilized powder is dissolved. The reconstituted solution has a total volume of 10.5 mL. Withdraw 10.5 mL of reconstituted solution to obtain 500 mg. After reconstitution, the final concentration is 47.6 mg/mL.

Step 3: The reconstituted TEPEZZA solution must be further diluted in 0.9% Sodium Chloride Injection, USP prior to infusion. To prepare the diluted solution, use 100 mL infusion bags for a dose less than 1800 mg, and 250 mL infusion bags for a dose equal to or greater than 1800 mg. To maintain a constant volume in the infusion bag, a sterile syringe and needle should be used to remove the volume equivalent to the amount of the reconstituted TEPEZZA solution to be placed into the infusion bag. Discard the volume of 0.9% Sodium Chloride Injection, USP withdrawn.

Step 4: Withdraw the required volume from the reconstituted TEPEZZA vial(s) based on the patient's weight (in kg) and transfer into the intravenous bag containing 0.9% Sodium Chloride Injection, USP. Mix diluted solution by gentle inversion. Do not shake. If refrigerated prior to administration, allow the diluted solution to reach room temperature prior to infusion.

The product does not contain any preservative. The combined storage time of reconstituted TEPEZZA solution in the vial and the diluted solution in the infusion bag containing 0.9% Sodium Chloride Injection, USP is a total of 4 hours at room temperature 20°C to 25°C (68°F to 77°F) or up to 48 hours under refrigerated conditions 2°C to 8°C (36°F to 46°F) protected from light.

Parenteral drug products should be inspected visually for particulate matter and discoloration prior to administration, whenever solution and container permit. Upon reconstitution, TEPEZZA is a nearly colorless or slightly brown, clear to opalescent solution which is free of foreign particulate matter. Discard the solution if any particulate matter or discoloration are observed.

Do not freeze the reconstituted or diluted solution.

Discard vial(s) and all unused contents.

No incompatibilities between TEPEZZA and polyethylene (PE), polyvinyl chloride (PVC), polyurethane (PUR) or polyolefin (PO) bags and intravenous administration sets have been observed.

2.3 Administration

Administer the diluted solution intravenously over at least 90 minutes for the first two infusions. If well tolerated, the minimum time for subsequent infusions can be reduced to 60 minutes. If not well tolerated, the minimum time for subsequent infusions should remain at 90 minutes, and pre-medication is recommended for subsequent infusions.

Do not administer as an intravenous push or bolus. TEPEZZA should not be infused concomitantly with other agents.

3 DOSAGE FORMS AND STRENGTHS

For injection (intravenous infusion): 500 mg of teprotumumab as a white to off-white lyophilized powder in a single-dose vial for reconstitution and dilution.

4 CONTRAINDICATIONS

None.

5 WARNINGS AND PRECAUTIONS

5.1 Infusion Reactions

TEPEZZA may cause infusion reactions. Infusion reactions have been reported in approximately 4% of patients treated with TEPEZZA. Signs and symptoms of infusion-related reactions include transient increases in blood pressure, feeling hot, tachycardia, dyspnea, headache and muscular pain. Infusion reactions may occur during any of the infusions or within 1.5 hours after an infusion. Reported infusion reactions are usually mild or moderate in severity and can usually be successfully managed with corticosteroids and antihistamines. In patients who experience an infusion reaction, consideration should be given to pre-medicating with an antihistamine, antipyretic, corticosteroid and/or administering all subsequent infusions at a slower infusion rate.

5.2 Inflammatory Bowel Disease

TEPEZZA may cause an exacerbation of inflammatory bowel disease (IBD). IBD has been reported in some patients without a prior diagnosis of IBD [see Adverse Reactions (6.2)]. Monitor patients for signs and symptoms of IBD. If IBD exacerbation is suspected, discontinue use of TEPEZZA.

5.3 Hyperglycemia

Hyperglycemia or increased blood glucose may occur in patients treated with TEPEZZA. In the premarketing clinical trials, 10% of patients (two-thirds of whom had preexisting diabetes or impaired glucose tolerance) experienced hyperglycemia [see Adverse Reactions (6.1)]. Hyperglycemic events should be controlled with medications for glycemic control, if necessary.

Assess patients for elevated blood glucose and symptoms of hyperglycemia prior to infusion and continue to monitor while on treatment with TEPEZZA. Ensure patients with hyperglycemia or preexisting diabetes are under appropriate glycemic control before and while receiving TEPEZZA.

5.4 Hearing Impairment Including Hearing Loss

TEPEZZA may cause severe hearing impairment including hearing loss, which in some cases may be permanent. Assess patients' hearing before, during, and after treatment with TEPEZZA and consider the benefit-risk of treatment with patients.

6 ADVERSE REACTIONS

The following clinically significant adverse reactions are described elsewhere in the labeling:

- Infusion Reactions [see Warnings and Precautions (5.1)]
- Inflammatory Bowel Disease [see Warnings and Precautions (5.2)]
- Hyperglycemia [see Warnings and Precautions (5.3)]
- Hearing Impairment Including Hearing Loss [see Warnings and Precautions (5.4)]

6.1 Clinical Trials Experience

Because clinical trials are conducted under widely varying conditions, adverse reaction rates observed in the clinical trials of a drug cannot be directly compared to rates in the clinical trials of another drug and may not reflect the rates observed in practice.

The safety of TEPEZZA was evaluated in two premarketing randomized, double-masked, placebo-controlled clinical trials (Study 1 [NCT01868997] and Study 2 [NCT03298867]) consisting of 170 patients with Thyroid Eye Disease (84 received TEPEZZA and 86 received placebo). Patients were treated with TEPEZZA (10 mg/kg for first infusion and 20 mg/kg for the remaining 7 infusions) or placebo given as an intravenous infusion every 3 weeks for a total of 8 infusions. The majority of patients completed 8 infusions (89% of TEPEZZA patients and 93% of placebo patients).

The most common adverse reactions (≥ 5%) that occurred at greater incidence in the TEPEZZA group than in the control group during the treatment period of Studies 1 and 2 are summarized in Table 1.

In addition, menstrual disorders (amenorrhea, metrorrhagia, dysmenorrhea) were reported in approximately 23% (5 of 22 patients) of menstruating women treated with TEPEZZA compared to 4% (1 of 25 patients) treated with placebo in the premarketing clinical trials.

Table 1. Adverse Reactions Occurring in 5% or More of Patients Treated with TEPEZZA and Greater Incidence than Placebo
Adverse Reactions | TEPEZZA N = 84 N (%) | Placebo N = 86 N (%)
Muscle spasms | 21 (25%) | 6 (7%)
Nausea | 14 (17%) | 8 (9%)
Alopecia | 11 (13%) | 7 (8%)
Diarrhea | 10 (12%) | 7 (8%)
Fatigue [Fatigue includes asthenia] | 10 (12%) | 6 (7%)
Hyperglycemia [Hyperglycemia includes blood glucose increase] | 8 (10%) | 1 (1%)
Hearing impairment [Hearing impairment including hearing loss (deafness, including sensorineural deafness, eustachian tube dysfunction, hyperacusis, hypoacusis, autophony and tinnitus)] | 8 (10%) | 0
Dysgeusia | 7 (8%) | 0
Headache | 7 (8%) | 6 (7%)
Dry skin | 7 (8%) | 0
Weight decreased | 5 (6%) | 0
Nail disorder [Nail disorder (includes nail discoloration, nail disorder and onychoclasis)] | 4 (5%) | 0

In clinical trials, gastrointestinal complaints including exacerbation of inflammatory bowel disease were reported.

In two postapproval trials, the following were the adverse reactions occurring ≥ 5% of participants treated with TEPEZZA during the double-masked treatment period: muscle spasms (29%), hearing impairment (19%), hyperglycemia (18%) diarrhea (16%), fatigue (13%), headache (13%), alopecia (10%), dry skin (10%), dysgeusia (9%), ear discomfort (9%), and nail disorder (6%).

6.2 Postmarketing Experience

The following adverse reactions have been identified during postapproval use of TEPEZZA. Because these reactions are reported voluntarily from a population of uncertain size, it is not always possible to reliably estimate their frequency or establish a causal relationship to drug exposure.

Gastrointestinal Disorders: bowel perforation, exacerbation of inflammatory bowel disease (IBD), including patients without a prior diagnosis of IBD

Metabolism and Nutrition Disorders: diabetic ketoacidosis, hyperosmolar hyperglycemic state (HHS)

Otologic: severe hearing impairment including hearing loss, which in some cases may be permanent

8 USE IN SPECIFIC POPULATIONS

8.1 Pregnancy

Risk Summary

Based on findings in animals and its mechanism of action inhibiting insulin-like growth factor-1 receptor (IGF-1R) signaling, TEPEZZA may cause fetal harm when administered to a pregnant woman. Adequate and well-controlled studies with TEPEZZA have not been conducted in pregnant women. There are insufficient data with TEPEZZA use in pregnant women to inform any drug associated risks for adverse developmental outcomes. Cynomolgus monkeys dosed once weekly with teprotumumab during pregnancy resulted in placental changes, decreased fetal growth during pregnancy, decreased fetal size and weight, and multiple external and skeletal abnormalities in offspring. Teprotumumab exposure may lead to an increase in fetal loss [see Data]. Therefore, TEPEZZA should not be used in pregnancy, and appropriate forms of contraception should be implemented prior to initiation, during treatment and for 6 months following the last dose of TEPEZZA. Women of childbearing age should have a pregnancy test performed by their doctor before starting treatment with TEPEZZA. If the patient becomes pregnant during treatment, TEPEZZA should be discontinued and the patient advised of the potential risk to the fetus.

The background rate of major birth defects and miscarriage is unknown for the indicated population. In the U.S. general population, the estimated background risks of major birth defects and miscarriage in clinically recognized pregnancies are 2-4% and 15-20%, respectively.

Data

Animal Data

In an abridged pilot embryo-fetal development study, seven pregnant cynomolgus monkeys were dosed intravenously at one dose level of teprotumumab, 75 mg/kg (2.8-fold the maximum recommended human dose (MRHD) based on AUC) once weekly from gestation day 20 through the end of gestation. The incidence of abortion was higher for the teprotumumab treated group compared to the control group. Teprotumumab caused decreased fetal growth during pregnancy, decreased fetal size and weight at caesarean section, decreased placental weight and size, and decreased amniotic fluid volume. Multiple external and skeletal abnormalities were observed in each exposed fetus, including: misshapen cranium, closely set eyes, micrognathia, pointing and narrowing of the nose, and ossification abnormalities of skull bones, sternebrae, carpals, tarsals and teeth. The test dose, 75 mg/kg of teprotumumab, was the maternal no observed adverse effect level (NOAEL).

Based on mechanism of action inhibiting IGF-1R, postnatal exposure to teprotumumab may cause harm.

8.2 Lactation

Risk Summary

There is no information regarding the presence of TEPEZZA in human milk, the effects on the breast-fed infant or the effects on milk production.

8.3 Females and Males of Reproductive Potential

Contraception

Females

Based on its mechanism of action inhibiting IGF-1R, TEPEZZA may cause fetal harm when administered to a pregnant woman [see Use in Specific Populations (8.1)]. Advise females of reproductive potential to use effective contraception prior to initiation, during treatment with TEPEZZA and for 6 months after the last dose of TEPEZZA.

8.4 Pediatric Use

Safety and effectiveness have not been established in pediatric patients.

8.5 Geriatric Use

Of the 171 patients in the two randomized trials, 15% were 65 years of age or older; the number of patients 65 years or older was similar between treatment groups. No overall differences in efficacy or safety were observed between patients 65 years or older and younger patients (less than 65 years of age).

10 OVERDOSAGE

No information is available for patients who have received an overdosage.

11 DESCRIPTION

Teprotumumab-trbw, an insulin-like growth factor-1 receptor inhibitor (IGF-1R), is a fully human IgG1 monoclonal antibody produced in Chinese hamster ovary (CHO-DG44) cells. It has a molecular weight of approximately 148 kilodaltons.

TEPEZZA (teprotumumab-trbw) for injection is supplied as a sterile, preservative-free, white to off-white, lyophilized powder for intravenous infusion. Each single-dose vial delivers 500 mg of teprotumumab-trbw, histidine (7.82 mg), L-histidine hydrochloride monohydrate (33.43 mg), polysorbate 20 (1.05 mg), and trehalose (898.43 mg). After reconstitution with 10 mL of Sterile Water for Injection, USP, the final concentration is 47.6 mg/mL with a pH of 5.5.

12 CLINICAL PHARMACOLOGY

12.1 Mechanism of Action

Teprotumumab-trbw's mechanism of action in patients with Thyroid Eye Disease has not been fully characterized. Teprotumumab-trbw binds to IGF-1R and blocks its activation and signaling.

12.2 Pharmacodynamics

No formal pharmacodynamic studies have been conducted with teprotumumab-trbw.

12.3 Pharmacokinetics

The pharmacokinetics of teprotumumab-trbw was described by a two compartment population PK model based on data from 40 patients with Thyroid Eye Disease receiving an initial intravenous infusion of 10 mg/kg, followed by infusions of 20 mg/kg TEPEZZA every 3 weeks in one clinical trial. Following this regimen, the mean (± standard deviation) estimates for steady-state area under the concentration curve (AUC), peak (Cmax), and trough (Ctrough) concentrations of teprotumumab-trbw were 138 (± 34) mg∙hr/mL, 632 (± 139) mcg/mL, and 176 (± 56) mcg/mL, respectively.

Distribution

Following the recommended TEPEZZA dosing regimen, the population PK estimated mean (± standard deviation) for central and peripheral volume of distribution of teprotumumab-trbw were 3.26 (± 0.87) L and 4.32 (± 0.67) L, respectively. The mean (± standard deviation) estimated inter-compartment clearance was 0.74 (± 0.16) L/day.

Elimination

Following the recommended TEPEZZA dosing regimen, the population PK estimated mean (± standard deviation) for the clearance of teprotumumab-trbw was 0.27 (± 0.08) L/day and for the elimination half-life was 20 (± 5) days.

Metabolism

Metabolism of teprotumumab-trbw has not been fully characterized. However, teprotumumab-trbw is expected to undergo metabolism via proteolysis.

Specific Populations

No clinically significant differences in the pharmacokinetics of teprotumumab-trbw were observed following administration of TEPEZZA based on patient's age (18-80 years), gender, race/ethnicity (103 White, 10 Black, and 3 Asian), weight (46-169 kg), mild to moderate renal impairment (creatinine clearance 30 to 89 mL/min estimated by Cockcroft-Gault Equation), bilirubin levels (2.7-24.3 mcmol/L), aspartate aminotransferase (AST) levels (11-221 U/L), or alanine aminotransferase (ALT) levels (7-174 U/L). The effect of hepatic impairment on the pharmacokinetics of teprotumumab-trbw is unknown.

Drug Interactions

No studies evaluating the drug interaction potential of TEPEZZA have been conducted.

12.6 Immunogenicity

The observed incidence of anti-drug antibody is highly dependent on the sensitivity and specificity of the assay. Differences in assay methods preclude meaningful comparisons of the incidence of anti-drug antibody in the studies described below with the incidence of anti-drug antibodies in other studies, including those of TEPEZZA.

In a randomized placebo-controlled study, HZNP-TEP-301, where active TED patients were administered placebo or TEPEZZA over a 24-week period, 2.4% (1 of 42) of placebo and 0% (0 of 41) of TEPEZZA treated patients tested positive for anti-teprotumumab antibodies at post-baseline visits.

Because of the low occurrence of anti-teprotumumab antibodies, the effect of these antibodies on the pharmacokinetics, pharmacodynamics, safety, and/or effectiveness of teprotumumab products is unknown.

13 NONCLINICAL TOXICOLOGY

13.1 Carcinogenesis, Mutagenesis, Impairment of Fertility

Carcinogenesis

The carcinogenic potential of TEPEZZA has not been evaluated in long-term animal studies.

Mutagenesis

The genotoxic potential of TEPEZZA has not been evaluated.

Impairment of Fertility

Fertility studies have not been performed with TEPEZZA.

14 CLINICAL STUDIES

TEPEZZA was evaluated in 2 randomized, double-masked, placebo-controlled studies in 171 patients with Thyroid Eye Disease: Study 1 (NCT01868997) and Study 2 (NCT03298867). Patients were randomized to receive TEPEZZA or placebo in a 1:1 ratio. Patients were given intravenous infusions (10 mg/kg for first infusion and 20 mg/kg for the remaining 7 infusions) every 3 weeks for a total of 8 infusions. Patients had a clinical diagnosis of Thyroid Eye Disease with symptoms and were euthyroid or had thyroxine and free triiodothyronine levels less than 50% above or below normal limits. Prior surgical treatment for Thyroid Eye Disease was not permitted. Proptosis ranged from 16 to 33 mm and 125 patients (73%) had diplopia at baseline.

A total of 84 patients were randomized to TEPEZZA and 87 patients were randomized to placebo. The median age was 52 years (range 20 to 79 years), 86% were White, 9% were Black or African-American, 4% were Asian and 1% identified as Other. The majority (73%) were female. At baseline, 27% of patients were smokers.

The proptosis responder rate at week 24 was defined as the percentage of patients with ≥ 2 mm reduction in proptosis in the study eye from baseline, without deterioration in the non-study eye (≥ 2 mm increase) in proptosis. Additional evaluations included signs and symptoms of Thyroid Eye Disease including pain, gaze evoked orbital pain, swelling, eyelid erythema, redness, chemosis, inflammation, clinical activity score and assessments of functional vision and patient appearance. Results for proptosis are found in Table 2.

Table 2. Efficacy Results in Patients with Thyroid Eye Disease in Study 1 and 2
 | Study 1 |  |  | Study 2
 | Teprotumumab (N = 42) | Placebo (N = 45) | Difference (95% CI) | Teprotumumab (N = 41) | Placebo (N = 42) | Difference (95% CI)
Proptosis responder rate at week 24, % (n) [Difference and its corresponding 95% Confidence Interval (CI) is based on a weighted average of the difference within each randomization stratum (tobacco user, tobacco non-use) using CMH weights.] | 71% (30) | 20% (9) | 51% (33, 69) | 83% (34) | 10% (4) | 73% (59, 88)
Proptosis (mm) average change from baseline through week 24, LS Mean (SE) [Results were obtained from an MMRM with an unstructured covariance matrix and including treatment, smoking status, baseline value, visit, treatment by visit, and visit by baseline value interaction as fixed effects. A change from baseline of 0 was imputed at the first post-baseline visit for any subject without a post baseline value.] | -2.5 (0.2) | -0.2 (0.2) | -2.3 (-2.8, -1.8) | -2.8 (0.2) | -0.5 (0.2) | -2.3 (-2.8, -1.8)

In Study 2, improvement of proptosis as measured by mean change from Baseline was observed as early as 6 weeks and continued to improve through week 24 as shown in Figure 1. Similar results were seen in Study 1.

Figure 1. Change from Baseline in Proptosis over 24 Weeks in Study 2

P < 0.01 at each timepoint

TEPEZZA also led to improvement in the less severely impacted "fellow" eye.

Diplopia (double vision) was evaluated in a subgroup of patients that had diplopia at baseline in Study 1 and 2. Results are shown in Table 3.

Table 3. Diplopia in Patients with Thyroid Eye Disease in Study 1 and 2
Parameter | TEPEZZA (n = 66) | Placebo (n = 59)
Diplopia
Responder rate [Diplopia was evaluated on a 4-point scale where scores ranged from 0 for no diplopia to 3 for constant diplopia. A diplopia responder was defined as a patient with baseline diplopia > 0 and a score of 0 at week 24.] at week 24, % (n) | 53% (35) | 25% (15)
P < 0.01

Following discontinuation of treatment in Study 1, 53% of patients (16 of 30 patients) who were proptosis responders at week 24 maintained proptosis response 51 weeks after the last TEPEZZA infusion. 67% of patients (12 of 18) who were diplopia responders at week 24 maintained diplopia response 51 weeks after the last TEPEZZA infusion.

Subgroups

Examination of age and gender subgroups did not identify differences in response to TEPEZZA among these subgroups. Reduction in proptosis was similar between smokers and non-smokers in both studies.

16 HOW SUPPLIED/STORAGE AND HANDLING

TEPEZZA (teprotumumab-trbw) for injection is a sterile, preservative-free, white to off-white lyophilized powder available as follows:

Carton containing one 500 mg single-dose vial | NDC 75987-130-15

STORAGE AND HANDLING

Refrigerate at 2°C to 8°C (36°F to 46°F) in original carton until time of use to protect from light. Do not freeze.

17 PATIENT COUNSELING INFORMATION

Embryo-Fetal Toxicity

- Advise females of reproductive potential that TEPEZZA can cause harm to a fetus and to inform their healthcare provider of a known or suspected pregnancy.
- Educate and counsel females of reproductive potential about the need to use effective contraception prior to initiation, during treatment with TEPEZZA and for 6 months after the last dose of TEPEZZA.

Infusion-related reactions

- Advise patients that TEPEZZA may cause infusion reactions that can occur at any time. Instruct patients to recognize the signs and symptoms of infusion reaction and to contact their healthcare provider immediately for signs or symptoms of potential infusion-related reactions.

Inflammatory Bowel Disease

- Advise patients on the risk of inflammatory bowel disease (IBD) including patients with or without a prior diagnosis of IBD. Advise patients to seek medical advice immediately if they experience diarrhea, with or without blood or rectal bleeding, associated with abdominal pain or cramping/colic, fecal urgency, tenesmus or incontinence.

Hyperglycemia

- Advise patients on the risk of hyperglycemia and, if diabetic, discuss with healthcare provider to adjust glycemic control measures including medications as appropriate. Encourage compliance with glycemic control.

Hearing Impairment Including Hearing Loss

- Advise patients that TEPEZZA may cause severe hearing impairment including hearing loss, which in some cases may be permanent. Instruct patients to contact their healthcare provider if they experience any signs or symptoms of hearing impairment or any changes in hearing.

TEPEZZA (teprotumumab-trbw)

Manufactured by:
Horizon Therapeutics Ireland DAC
Dublin, Ireland U.S. License No. 2022

Patent: http://pat.amgen.com/tepezza/

© 2025 Amgen Inc. All rights reserved
1-800-772-6436

1XXXXXX-V9

PRINCIPAL DISPLAY PANEL - 500 mg Vial Carton

NDC-75987-130-15

TEPEZZA®
(teprotumumab-trbw)
for Injection

500 mg/vial

For Intravenous Infusion Only
Reconstitute and Further Dilute Prior to Use

Single-dose vial. Discard unused portion.

AMGEN